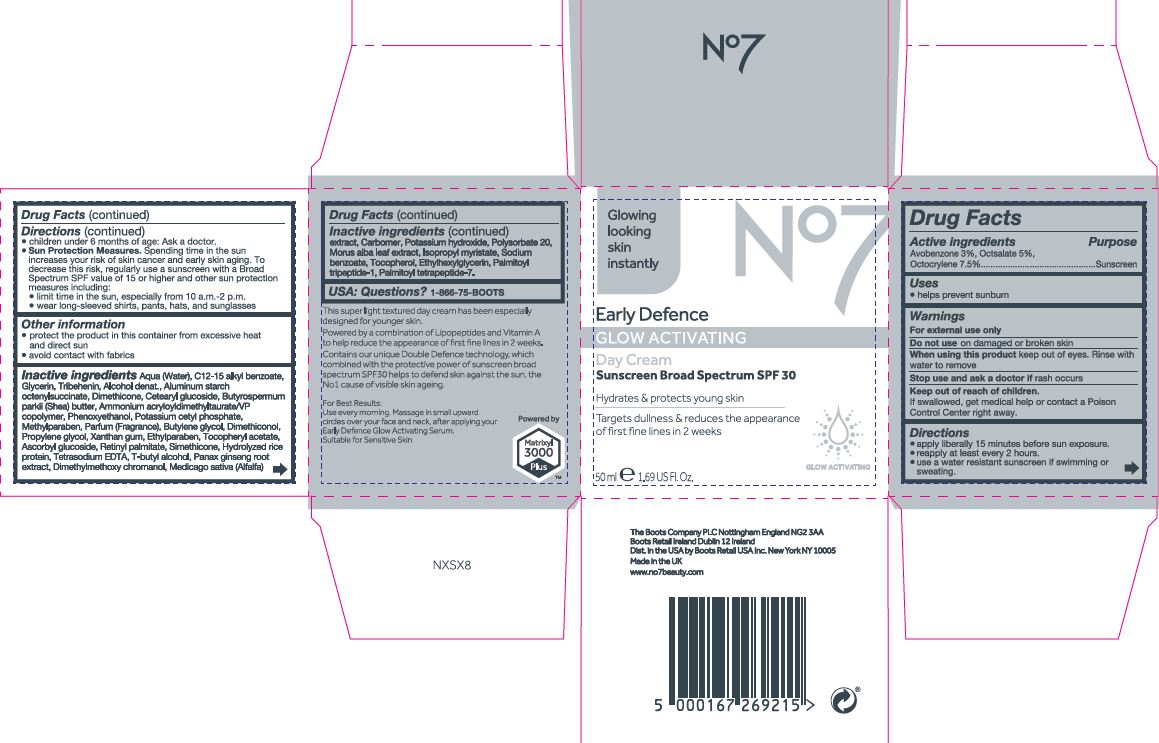 DRUG LABEL: No7 Early Defence Glow Activating Day Cream
NDC: 11489-145 | Form: CREAM
Manufacturer: BCM Ltd
Category: otc | Type: HUMAN OTC DRUG LABEL
Date: 20190924

ACTIVE INGREDIENTS: AVOBENZONE 1.5 g/1 g; OCTISALATE 2.5 g/1 g; OCTOCRYLENE 3.75 g/1 g
INACTIVE INGREDIENTS: WATER; GLYCERIN; ALUMINUM STARCH OCTENYLSUCCINATE; CETEARYL GLUCOSIDE; DIMETHICONE; TRIBEHENIN; AMMONIUM ACRYLOYLDIMETHYLTAURATE/VP COPOLYMER; PHENOXYETHANOL; SHEA BUTTER; POTASSIUM CETYL PHOSPHATE; BUTYLENE GLYCOL; DIMETHICONOL (100000 CST); PROPYLENE GLYCOL; METHYLPARABEN; ETHYLPARABEN; XANTHAN GUM; PANAX GINSENG ROOT OIL; VITAMIN A PALMITATE; ASCORBYL GLUCOSIDE; EDETATE SODIUM; TERT-BUTYL ALCOHOL; DIMETHYLMETHOXY CHROMANOL; POLYSORBATE 20; MEDICAGO SATIVA LEAF; POTASSIUM HYDROXIDE; CARBOMER 940; MORUS ALBA LEAF; ISOPROPYL MYRISTATE; SODIUM BENZOATE; ETHYLHEXYLGLYCERIN; TOCOPHEROL; PALMITOYL TRIPEPTIDE-1; PALMITOYL TETRAPEPTIDE-7

No7 Early Defence Glow Activating Day Cream Sunscreen Broad Spectrum SPF 30

Carton Active Ingredients Section

Active ingredients

Avobenzone 3%, Octisalate 5%, Octocrylene 7.5%

Purpose

Sunscreen

Uses

- helps prevent sunburn

Warnings

For external use only

Do not use on damaged or broken skin

When using this product keep out of eyes. Rinse with water to remove.

Ask a doctor

Stop use and ask a doctor if rash occurs

Keep out of reach of children

If swallowed, get medical help or contact a Poison Control Center right away.

Directions

- apply liberally 15 minutes before sun exposure.

- reapply at least every 2 hours.

- use a water resistant sunscreen if swimming or sweating.

- children under 6 months of age: Ask a doctor.

- Sun Protection Measures. Spending time in the sun increases your risk of skin cancer and early skin aging. To decrease this risk, regularly use a sunscreen with a Broad Spectrum SPF value of 15 or higher and other sun protection measures including:

- limit time in the sun, especially from 10 a.m-2 p.m.

- wear long-sleeved shirts, pants, hats and sunglasses

Storage

Other information

- protect the product in this container from excessive heat and direct sun

- avoid contact with fabrics

Inactive ingredients

Aqua (Water), C12-15 alkyl benzoate, Glycerin, Tribehenin, Alcohol denat., Aluminum starch octenylsuccinate, Dimethicone, Cetearyl glucoside, Butyrospermum parkii (Shea) butter, Ammonium acryloydimethyltaurate/VP copolymer, Phenoxyethanol, Potassium cetyl phosphate, Methylparaben, Parfum (Fragrance), Butylene glycol, Dimethiconol, Propylene glycol, Xanthan gum, Ethylparaben, Tocopheryl acetate, Ascorbyl glucoside, Retinyl palmitate, Hydrolyzed rice protein, Tetrasodium EDTA, T-butyl alcohol, Panax ginseng root extract, Dimethylmethoxy chromanol, Medicago sativa (Alfalfa) extract, Carbomer, Potassium hydroxide, Polysorbate 20, Morus alba leaf extract, Isopropyl myristate, Sodium benzoate, Tocopherol, Ethylhexylglycerin, Palmitoyl tripeptide-1, Palmitoyl tetrapeptide-7.

Description

Glowing looking skin instantly

No7 Early Defence GLOW ACTIVATING Day Cream Sunscreen Broad Spectrum SPF 30

Hydrates & protects young skin

Targets dullness & reduces the appearance of first fine lines in 2 weeks

GLOW ACTIVATING

50 ml e 1.69 US Fl. Oz.

This super light textured day cream has been especially designed for younger skin.

Powered by a combination of Lipopeptides and Vitamin A to help reduce the appearance of first lines in 2 weeks.

Contains our unique Double Defence technology, which combined with the protective power of sunscreen broad spectrum SPF30 helps to defend skin against the sun, the No1 cause of visible skin ageing.

For Best Results: Use every morning. Massage in small upward cicles over your face and neck, after applying your Early Defence Glow Activating Serum.

Suitable for Sensitive Skin

Powered by Matrixyl 3000 PlusTM

Questions

USA: Questions? 1-866-75-BOOTS

PATIENT COUNSELING INFORMATION

The Boots Company PLC Notingham England NG2 3AA

Boos Retail Ireland Dublin 12 Ireland

Dist. in the USA by Boots Retail USA Inc. New York NY 10005

Made in the UK

www.no7beauty.com

Carton